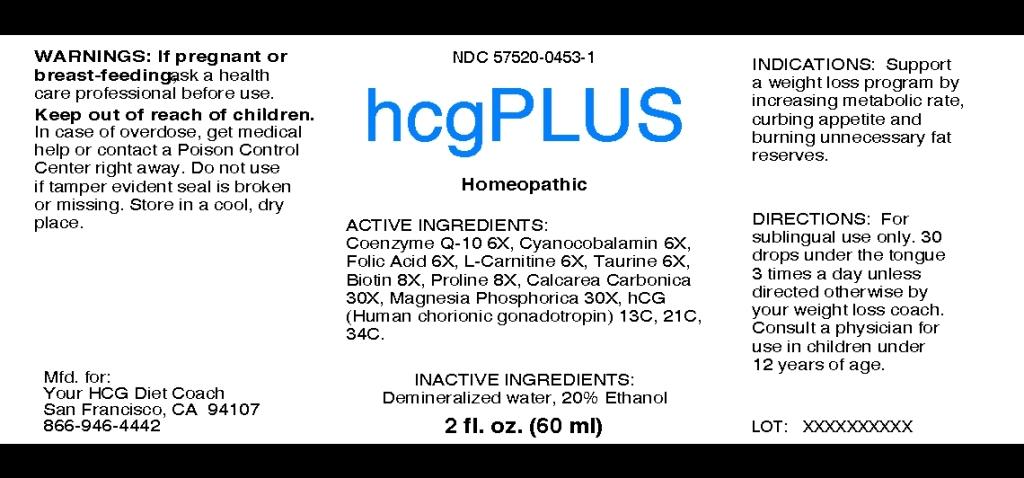 DRUG LABEL: hcgPLUS
NDC: 57520-0453 | Form: LIQUID
Manufacturer: Apotheca Company
Category: homeopathic | Type: HUMAN OTC DRUG LABEL
Date: 20100803

ACTIVE INGREDIENTS: UBIDECARENONE 6 [hp_X]/1 mL; CYANOCOBALAMIN 6 [hp_X]/1 mL; FOLIC ACID 6 [hp_X]/1 mL; LEVOCARNITINE 6 [hp_X]/1 mL; TAURINE 6 [hp_X]/1 mL; BIOTIN 8 [hp_X]/1 mL; PROLINE 8 [hp_X]/1 mL; OYSTER SHELL CALCIUM CARBONATE, CRUDE 30 [hp_X]/1 mL; MAGNESIUM PHOSPHATE, DIBASIC TRIHYDRATE 30 [hp_X]/1 mL; SOMATROPIN 34 [hp_C]/1 mL
INACTIVE INGREDIENTS: WATER; ALCOHOL

hcgPlus

ACTIVE INGREDIENT

ACTIVE INGREDIENTS: Coenzyme Q-10 6X, Cyanocobalamin 6X, Folic Acid 6X, L-carnitine 6X, Taurine 6X, Biotin 8X, Proline 8X, Calcarea carbonica 30X, Magnesia phosphorica 30X, hCG 13C, 21C, 34C.

PURPOSE

INDICATIONS: Support a weight loss program by increasing metabolic rate, curbing appetite and burning unnecessary fat reserves.

WARNINGS

WARNINGS: If pregnant or breast-feeding, ask a health care professional before use.

Keep out of reach of children. In case of overdose, get medical help or contact a Poison Control Center right away.

Do not use if tamper evident seal is broken or missing. Store in a cool, dry place.

DOSAGE AND ADMINISTRATION

DIRECTIONS: For sublingual use only. 30 drops under the tongue 3 times a day unless directed otherwise by your weight loss coach. Consult a physician for use in children under 12 years of age.

INACTIVE INGREDIENTS: Demineralized water, 20% Ethanol.

QUESTIONS

MFD. for:

Your HCG Diet Coach

San Francisco, CA 94107

866-946-4442

PACKAGE LABEL

hcgPLUS

Homeopathic

2 fl. oz. (60 ml)